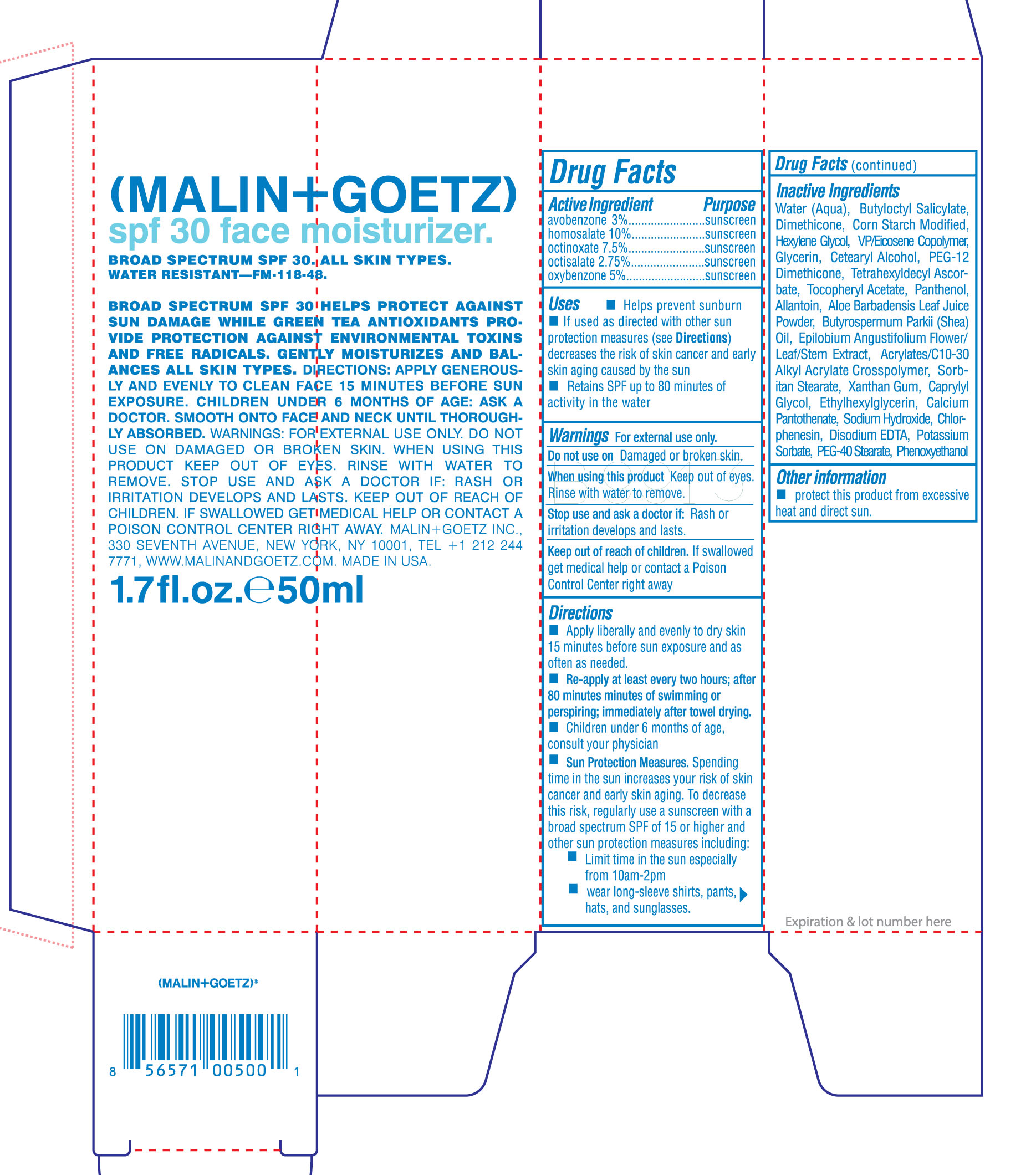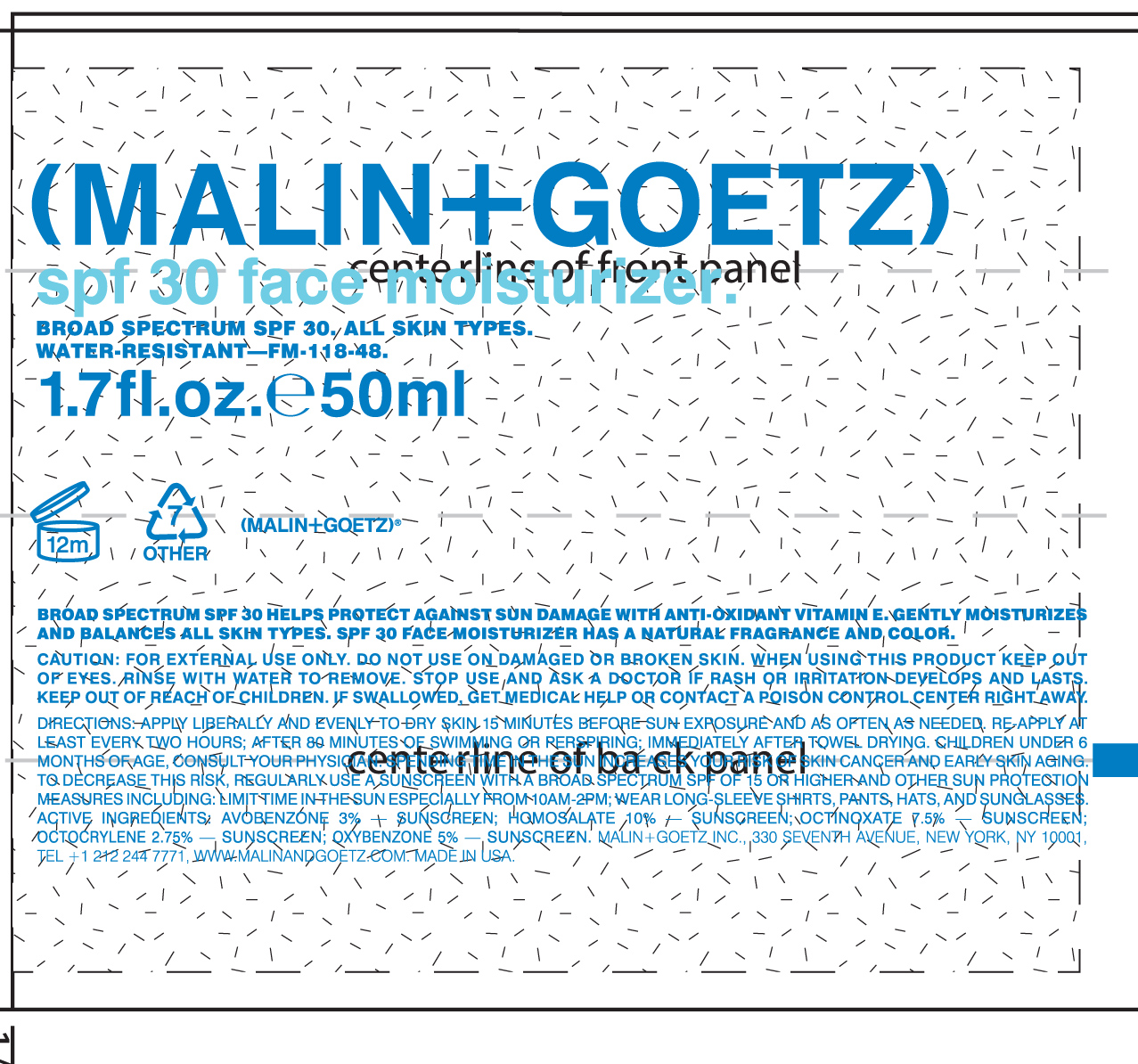 DRUG LABEL: SPF 30 face Moisturizer
NDC: 53634-255 | Form: LOTION
Manufacturer: Malin and Goetz Inc
Category: otc | Type: HUMAN OTC DRUG LABEL
Date: 20210126

ACTIVE INGREDIENTS: AVOBENZONE 3 g/100 mL; HOMOSALATE 10 g/100 mL; OCTINOXATE 7.5 g/100 mL; OCTISALATE 2.75 1/100 mL; OXYBENZONE 5 1/100 mL
INACTIVE INGREDIENTS: WATER; BUTYLOCTYL SALICYLATE; DIMETHICONE; MODIFIED CORN STARCH (1-OCTENYL SUCCINIC ANHYDRIDE); HEXYLENE GLYCOL; VINYLPYRROLIDONE/EICOSENE COPOLYMER; GLYCERIN; CETOSTEARYL ALCOHOL; PEG-12 DIMETHICONE; TETRAHEXYLDECYL ASCORBATE; .ALPHA.-TOCOPHEROL ACETATE; PANTHENOL; ALLANTOIN; ALOE FEROX LEAF; SHEANUT OIL; EPILOBIUM ANGUSTIFOLIUM FLOWERING TOP; CARBOMER COPOLYMER TYPE A (ALLYL PENTAERYTHRITOL CROSSLINKED); SORBITAN MONOSTEARATE; XANTHAN GUM; CAPRYLYL GLYCOL; ETHYLHEXYLGLYCERIN; CALCIUM PANTOTHENATE; SODIUM HYDROXIDE; CHLORPHENESIN; EDETATE DISODIUM ANHYDROUS; POTASSIUM SORBATE; PEG-40 STEARATE; PHENOXYETHANOL

SPF 30 Face Moisturizer

Active Ingredient Purpose

Avobenzone 3% sunscreen

Homosalate 10% sunscreen

Octinoxate 7.5% sunscreen

Octisalate 2.75% sunscreen

Oxybenzone 5% sunscreen

Uses

- Helps prevent sunburn

- If used as directed with other sun proctection measures (see Directions) decreases the risk of skin cancer and early skin aging caused by the sun
- Retains SPF up to 80 minutes of activity in the water

Keep out of reach of children. If swallowed get medical help or contact a Poison Control Center right away

Stop use and ask a doctor if: Rash or irritation develops and lasts.

Warnings For external use only.

Do not use on damaged or broken skin.

When using this product keep out of eyes. Rinse with water to remove.

Directions

- Apply liberally and evenly to dry skin 15 minutes before sun exposure and as often as needed.
- Re-apply at least every 2 hours; after 80 minutes of swimming or perspiring; immediately after towel drying.
- Children under 6 months of age, consult your physician
- Sun Protection Measures. Spending time in the sun increases your risk of skin cancer and early skin aging. To decrease this risk, regualarly use a sunscreen with a broad spectrum SPF of 15 or higher and other sun protection measures including:
- Limit time in the sun from 10am-2pm
- wear long sleeve shirts, pants, hats and sunglasses

INACTIVE INGREDIENT

Water(Aqua), Butyloctyl Salicylate, Dimethicone, Corn Start Modified, Hexylene Glycol, VP/Eicosene Copolymer, Glcyerin, Cetearyl Alcohol, PEG-12 Dimethicone, Tetrahexyldecyl Ascorbate, Tocopheryl Acetate, Panthenol, Allantoin, Aloe Barbadensis Leaf Juice Powder, Butyrospermum Parkii (shea) Oil, Epilobium Angustifolium Flower/leaf/stem extract, Acrylates/C10-30 Alkyl Acrylate Crosspolymer, Sorbitan Stearate, Xanthan Gum, Caprylyl Glycol, Ethylhexylglycerin, Calcium Pantothenate, Sodium Hydroxide, Chlorphenesin, Disodium EDTA, Potassium Sorbate, PEG-40 Stearate, Phenoxyethanol

PACKAGE LABEL

(Malin + Goetz)

SPF 30 Face Moisturizer

Broad Spectrum SPF 30 All skin types

Water Resistant

1.7 fl. oz. 50 ml